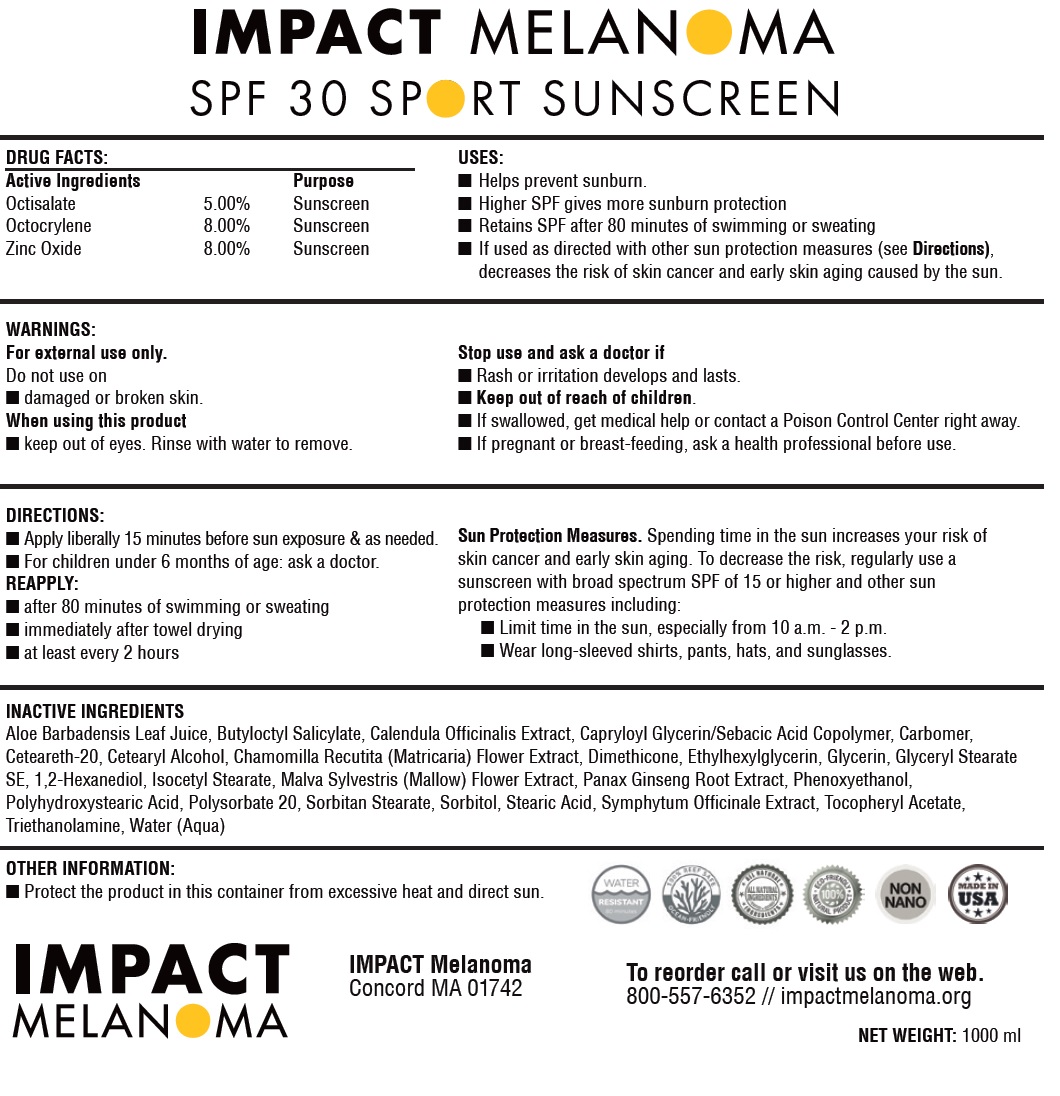 DRUG LABEL: Sunstation Sport Sunscreen SPF 30
NDC: 85528-592 | Form: CREAM
Manufacturer: Impact Melanoma Inc
Category: otc | Type: HUMAN OTC DRUG LABEL
Date: 20250424

ACTIVE INGREDIENTS: OCTISALATE 50 mg/1 mL; OCTOCRYLENE 80 mg/1 mL; ZINC OXIDE 80 mg/1 mL
INACTIVE INGREDIENTS: ALOE VERA LEAF; BUTYLOCTYL SALICYLATE; CALENDULA OFFICINALIS FLOWER; CARBOMER HOMOPOLYMER, UNSPECIFIED TYPE; CETEARETH-20; CETEARYL ALCOHOL; CHAMOMILE; DIMETHICONE; ETHYLHEXYLGLYCERIN; GLYCERIN; GLYCERYL STEARATE SE; 1,2-HEXANEDIOL; ISOCETYL STEARATE; MALVA SYLVESTRIS FLOWER; ASIAN GINSENG; PHENOXYETHANOL; POLYSORBATE 20; SORBITAN MONOSTEARATE; SORBITOL; STEARIC ACID; .ALPHA.-TOCOPHEROL ACETATE; TROLAMINE; WATER

Sunstation Sport Sunscreen SPF 30

Active Ingredients

Octisalate 5%
Octocrylene 8%
Zinc Oxide 8%

Purpose

Sunscreen

USES:

- Helps prevent sunburn.
- Higher SPF gives more sunburn protection
- Retains SPF after 80 minutes of swimming or sweating
- If used as directed with other sun protection measures (see Directions), decreases the risk of skin cancer and early skin aging caused by the sun.

WARNINGS:

For external use only.

Do not use

- on damaged or broken skin.

When using this product

- keep out of eyes. Rinse with water to remove.

Stop use and ask a doctor if

- Rash or irritation develops and lasts.

Keep out of reach of children.

If swallowed, get medical help, or contact a Poison Control Center right away.

If pregnant or breast-feeding,

ask a health professional before use.

DIRECTIONS:

- Apply liberally 15 minutes before sun exposure & as needed.
- For children under 6 months of age: ask a doctor.
- REAPPLY::
- after 80 minutes of swimming or sweating
- immediately after towel drying
- at least every 2 hours
- Sun Protection Measures.Spending time in the sun increases your risk of skin cancer and early skin aging. To decrease this risk, regularly use a sunscreen with broad spectrum SPF of 15 or higher and other sun protection measures including:
- Limit time in the sun, especially from 10 a.m. -2p.m.
- Wear long-sleeved shirts, pants, hats, and sunglasses.

INACTIVE INGREDIENTS:

Aloe Barbadensis Leaf Juice, Butyloctyl Salicylate, Calendula Officinalis Extract, Capryloyl Glycerin/Sebacic Acid Copolymer, Carbomer,
Ceteareth-20, Cetearyl Alcohol, Chamomilla Recutita (Matricaria) Flower Extract, Dimethicone, Ethylhexylglycerin, Glycerin, Glyceryl Stearate
SE, 1,2-Hexanediol, Isocetyl Stearate, Malva Sylvestris (Mallow) Flower Extract, Panax Ginseng Root Extract, Phenoxyethanol,
Polyhydroxystearic Acid, Polysorbate 20, Sorbitan Stearate, Sorbitol, Stearic Acid, Symphytum Officinale Extract, Tocopheryl Acetate,
Triethanolamine, Water (Aqua)

OTHER INFORMATION:

- Protect the product in this container from excessive heat and direct sun.